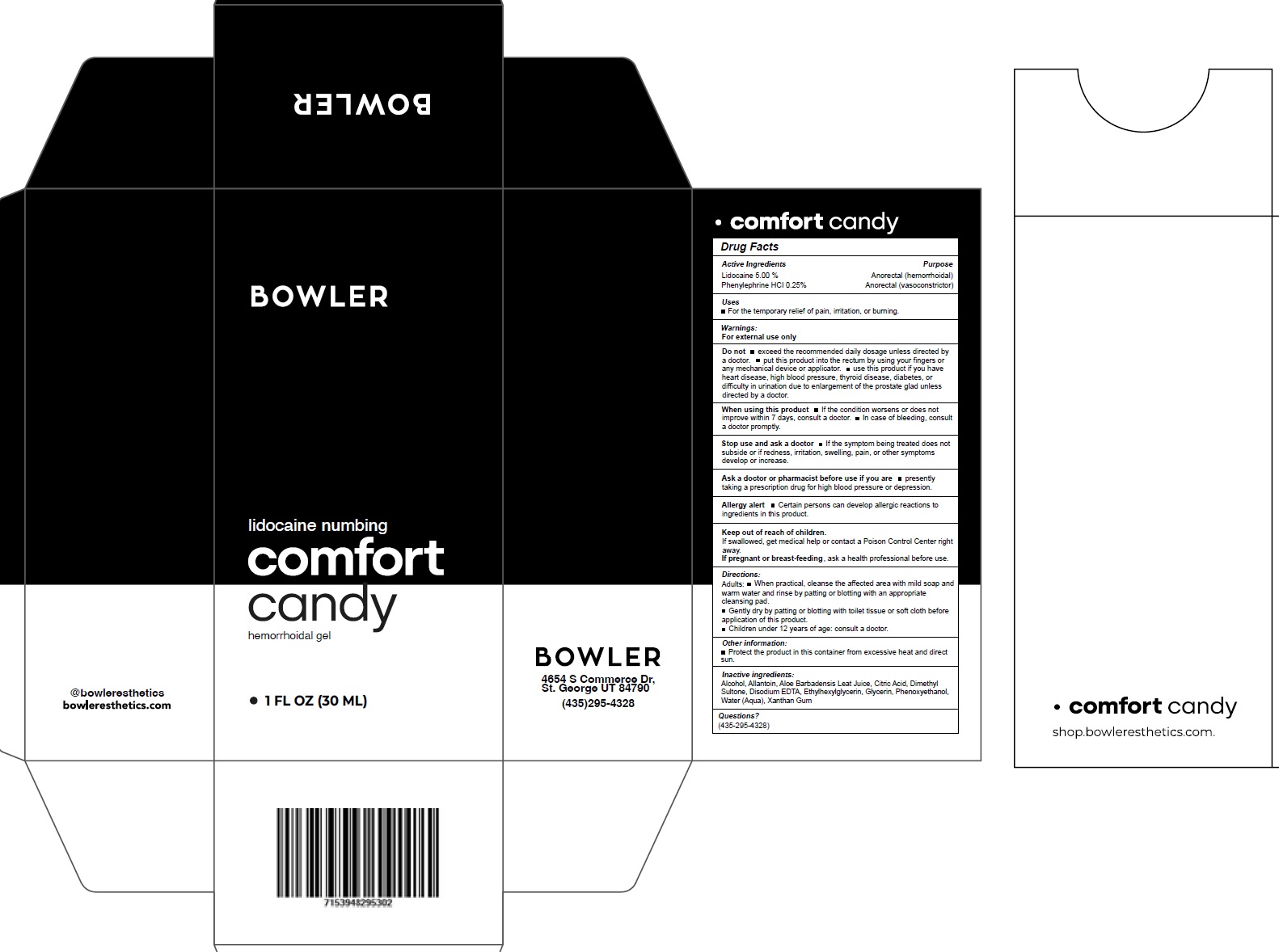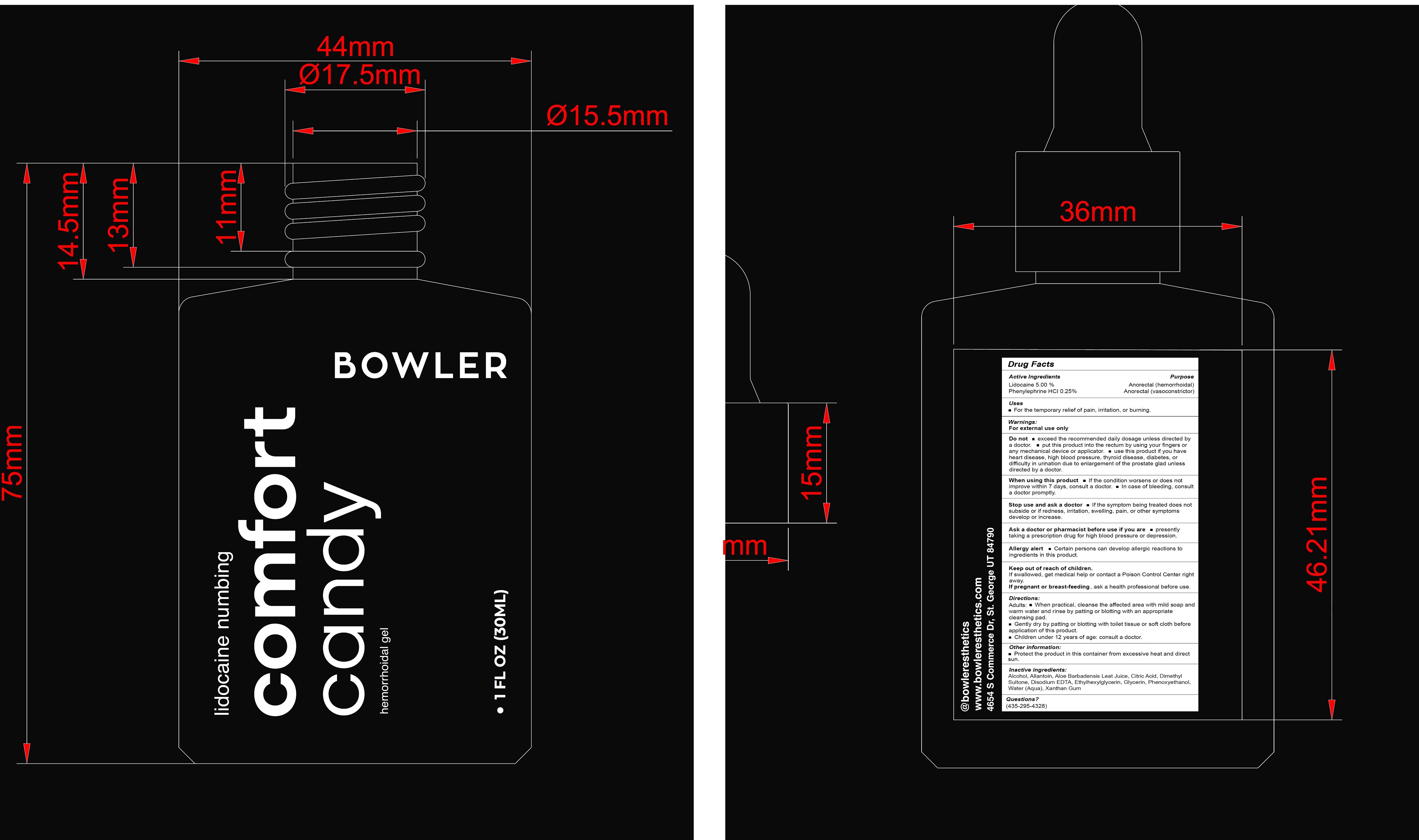 DRUG LABEL: Comfort Candy Hemorrhoidal
NDC: 85956-624 | Form: GEL
Manufacturer: BOWLER ESTHETICS, INC
Category: otc | Type: HUMAN OTC DRUG LABEL
Date: 20250723

ACTIVE INGREDIENTS: LIDOCAINE 50 mg/1 mL; PHENYLEPHRINE HYDROCHLORIDE 2.5 mg/1 mL
INACTIVE INGREDIENTS: ALCOHOL; ALLANTOIN; ALOE VERA LEAF JUICE; CITRIC ACID MONOHYDRATE; DIMETHYL SULFONE; EDETATE DISODIUM; ETHYLHEXYLGLYCERIN; GLYCERIN; PHENOXYETHANOL; WATER; XANTHAN GUM

Comfort Candy Hemorrhoidal Gel

Active Ingredients

Lidocaine 5.00 %
Phenylephrine Hcl 0.25%

Purpose

Anorectal (hemorrhoidal)
Anorectal (vasoconstrictor)

Uses

- For the temporary relief of pain, irritation, or burning.

Warnings:

For external use only

Do not

- exceed the recommended daily dosage unless directed by a doctor.
- put this product into the rectum by using your fingers or any mechanical device or applicator.
- use this product if you have heart disease, high blood pressure, thyroid disease, diabetes, or difficulty in urination due to enlargement of the prostate glad unless directed by a doctor.

When using this product

- If the condition worsens or does not improve within 7 days, consult a doctor.
- In case of bleeding, consult a doctor promptly.

Stop use and ask a doctor

- If the symptom being treated does not subside or if redness, irritation, swelling, pain, or other symptoms develop or increase.

Ask a doctor or pharmacist before use if you are

- presently taking a prescription drug for high blood pressure or depression.

Allergy alert

- Certain persons can develop allergic reactions to ingredients in this product.

Keep out of reach of children.

If swallowed, get medical help or contact a Poison Control Center right away.

If pregnant or breast-feeding ,

ask a health professional before use.

Directions:

Adults:

- When practical, cleanse the affected area with mild soap and warm water and rinse by patting or blotting with an appropriate cleansing pad.
- Gently dry by patting or blotting with toilet tissue or soft cloth before application of this product.
- Children under 12 years of age: consult a doctor.

Other information:

- Protect the product in this container from excessive heat and direct sun.

Inactive ingredients:

Alcohol, Allantoin, Aloe Barbadensis Leaf Juice, Citric Acid, Dimethyl Sulfone, Disodium EDTA, Ethylhexylglycerin, Glycerin, Phenoxyethanol, Water (Aqua), Xanthan Gum

Questions?

(435-295-4328)